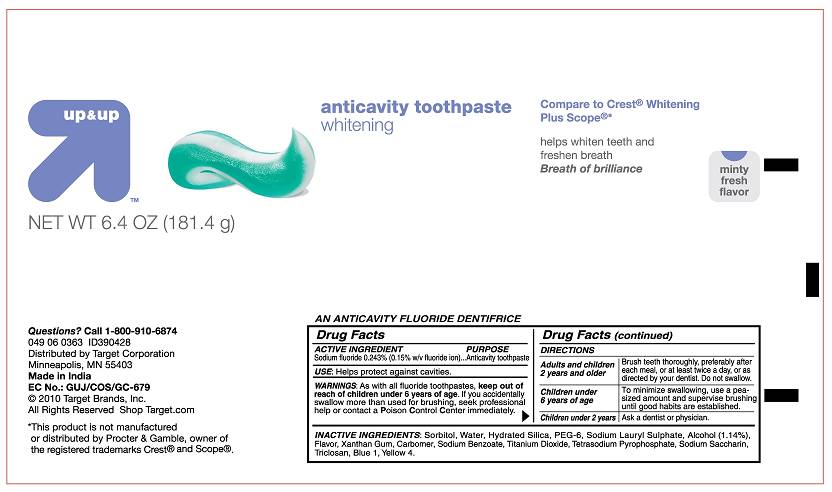 DRUG LABEL: Up and UP Anticavity Toothpaste Whitening Plus Mouthwash
NDC: 11673-090 | Form: PASTE, DENTIFRICE
Manufacturer: Target Corporation
Category: otc | Type: HUMAN OTC DRUG LABEL
Date: 20110531

ACTIVE INGREDIENTS: SODIUM FLUORIDE  2.43 mg/1 g
INACTIVE INGREDIENTS: SORBITOL; WATER; SILICON DIOXIDE  ; POLYETHYLENE GLYCOL 300  ; SODIUM LAURYL SULFATE  ; ALCOHOL 1.14 mg/1 g; XANTHAN GUM  ; CARBOMER 934  ; SODIUM BENZOATE  ; TITANIUM DIOXIDE  ; SODIUM PYROPHOSPHATE ; SACCHARIN SODIUM  ; TRICLOSAN; FD&C BLUE NO. 1  

Up and UP Anticavity Toothpaste Whitening

Active Ingredient

Sodium fluoride 0.243% (0.15% w/v fluoride ion)... Anticatity toothpaste

USE

Helps protect against cavities

WARNINGS

As with all fluoride toothpastes, keep out of reach of children under 6 years of age. If you accidentally swallow more than used for brushing, seek professional help or contact a Poison Control Center immediately.

Directions

Adults and children 2 years and older Brush teeth thoroughly, PREFERABLY AFTER EACH MEAL,or at least twice a day, or as directed by your dentist. DO NOT SWALLOW
Children under 6 years of age To minimize swallowing, use a pea-sized amount and supervise brushing until good habits are established.
Children under 2 years ASK A dentist or physician

Inactive Ingredients:

Sorbitol, Water, HYDRATED SILICA, PEG-6, Sodium Lauryl Sulphate, Alcohol (1.14%), Flavor, Xanthan Gum, Carbomer, Sodium Benzoate, Titanium Dioxide, Tetrasodium Pyrophosphate, Sodium Saccharin, Triclosan, Blue 1, Yellow 4.

PURPOSE

Anticatity toothpaste

KEEP OUT OF REACH OF CHILDREN